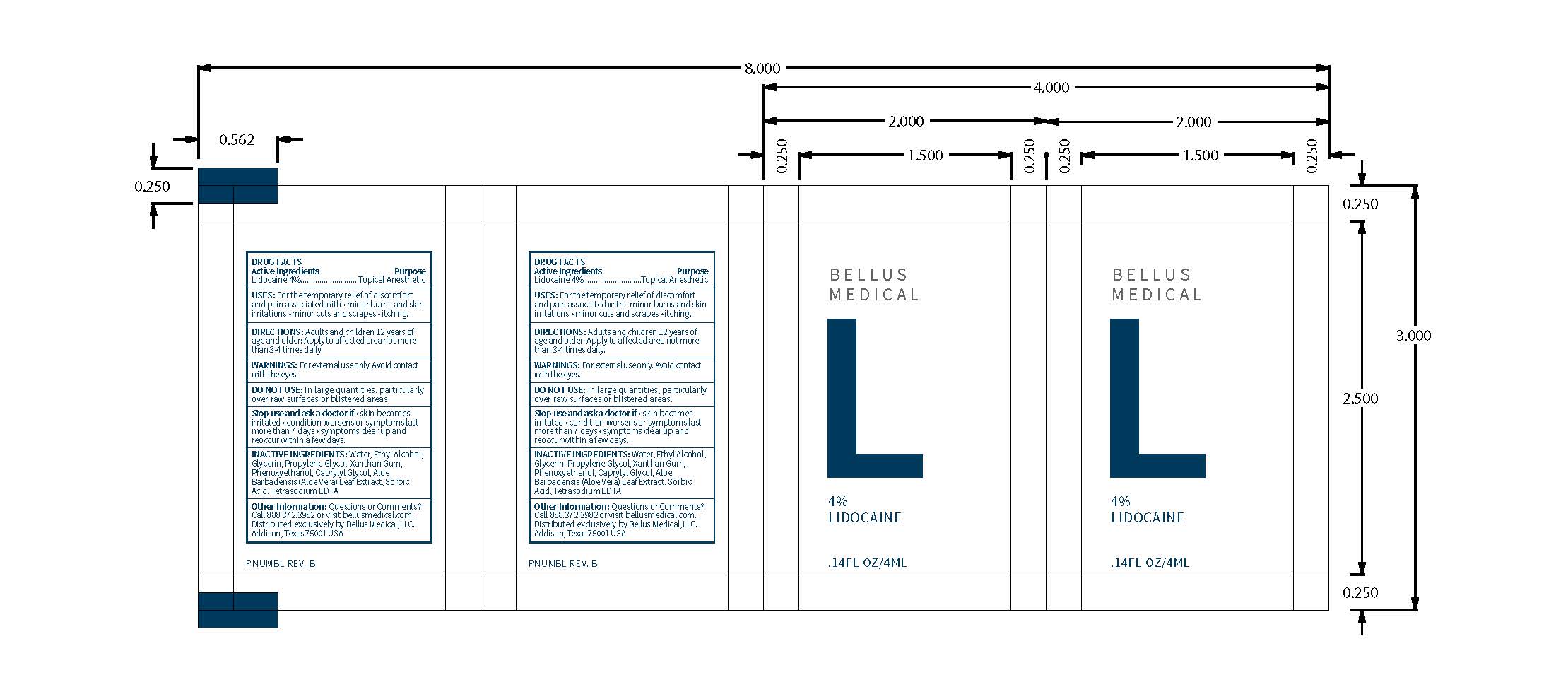 DRUG LABEL: Lidocaine
NDC: 71888-102 | Form: GEL
Manufacturer: Bellus Medical, LLC
Category: otc | Type: HUMAN OTC DRUG LABEL
Date: 20241118

ACTIVE INGREDIENTS: LIDOCAINE 4 g/100 mL
INACTIVE INGREDIENTS: WATER; ALCOHOL; GLYCERIN; PROPYLENE GLYCOL; XANTHAN GUM; ALOE VERA LEAF; CAPRYLYL GLYCOL; PHENOXYETHANOL; SORBIC ACID; EDETATE SODIUM

4% Lidocaine Gel

ACTIVE INGREDIENT

Lidocaine 4%

INACTIVE INGREDIENT

Water, Ethyl Alcohol, Glycerin, Propylene Glycol, Xanthan Gum, Phenoxyethanol, Caprylyl Glycol, Aloe Barbadensis (Aloe Vera) Leaf Extract, Sorbic Acid, Tetrasodium EDTA.

DOSAGE AND ADMINISTRATION

USES: For the temporary relief of discomfort and pain associated with

- Minor burns and skin irritations
- Minor cuts and scrapes
- Itching

DIRECTIONS: Adults and Children 12 years of age and older apply to affected area not more than 3-4 times daily.

WARNINGS

WARNINGS: For external use only. Avoid contact with the eyes.

DO NOT USE: In large quantities particularly over raw sources or blistered areas.

INDICATIONS AND USAGE

USES: For the temporary relief of discomfort and pain associated with

- Minor burns and skin irritations
- Minor cuts and scrapes
- Itching

DIRECTIONS: Adults and Children 12 years of age and older apply to affected area not more than 3-4 times daily.

PURPOSE

Topical Anesthetic

Keep put of reach of children.